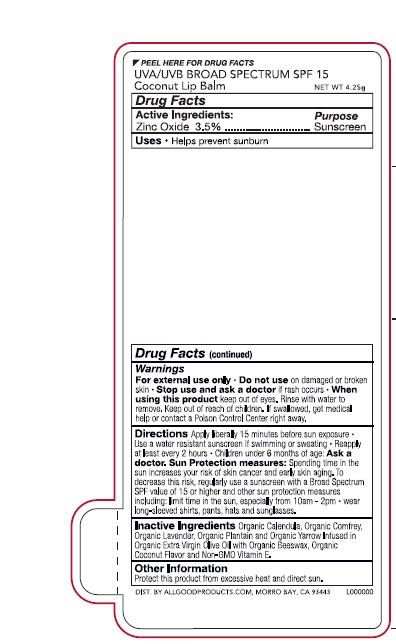 DRUG LABEL: Broad Spectrum SPF 15 Coconut Lip Balm
NDC: 65692-0307 | Form: STICK
Manufacturer: Raining Rose, Inc.
Category: otc | Type: HUMAN OTC DRUG LABEL
Date: 20231103

ACTIVE INGREDIENTS: ZINC OXIDE 35 mg/1 g
INACTIVE INGREDIENTS: CALENDULA OFFICINALIS FLOWER; COMFREY LEAF; LAVANDULA ANGUSTIFOLIA FLOWER; PLANTAGO MAJOR LEAF; ACHILLEA MILLEFOLIUM FLOWER; OLIVE OIL; YELLOW WAX; TOCOPHEROL

Broad Spectrum SPF 15 Coconut Lip Balm

DRUG FACTS

Active Ingredients:

Zinc Oxide 3.5%

Purpose

Sunscreen

Uses

- Helps prevent sunburn

Warnings

For External Use Only

- Do not use on damaged or broken skin

Stop use and as a doctor if rash occurs

- When using this product keep out of eyes. Rinse well with water to remove.

Keep out of reach of children.

If swallowed, get medical help or call a Poison Control Center right away.

DOSAGE AND ADMINISTRATION

Directions Apply liberally 15 minutes before sun exposure •
• Use a water resistant sunscreen if swimming or sweatinb •Reapply
at least every 2 hours • Children under 6 months of age: Ask a
doctor. Sun Protection Measures: Spending time in the sun
increases your risk of skin cancer and early skin aging. To
decrease this risk, regularly use a sunscreen with a Broad Spectrum SPF
value of 15 or higher and other protection measures
including: limit time in the sun, especially from 10a.m. - 2p.m. • wear
long-sleeved shirts, pants, hats and sunglasses.

Inactive Ingredients: Organic Calendula, Organic Comfrey,

Organic Lavender, Organic Plantain and Organic Yarrow Infused in

Organic Extra Virgin Olive Oil with Organic Beeswax, Organic

Coconut Flavor and Non-GMO Vitamin E.

Other Information

Protect this product from excessive heart and direct sun.

Product Package Labeling

UVA/UVB BROAD SPECTRUM SPF 15

Coconut Lip Balm

NET WT. 4.25g

DIST. BY ALLGOODPRODUCTS.COM, MORRO BAY, CA 93443 L000000

res